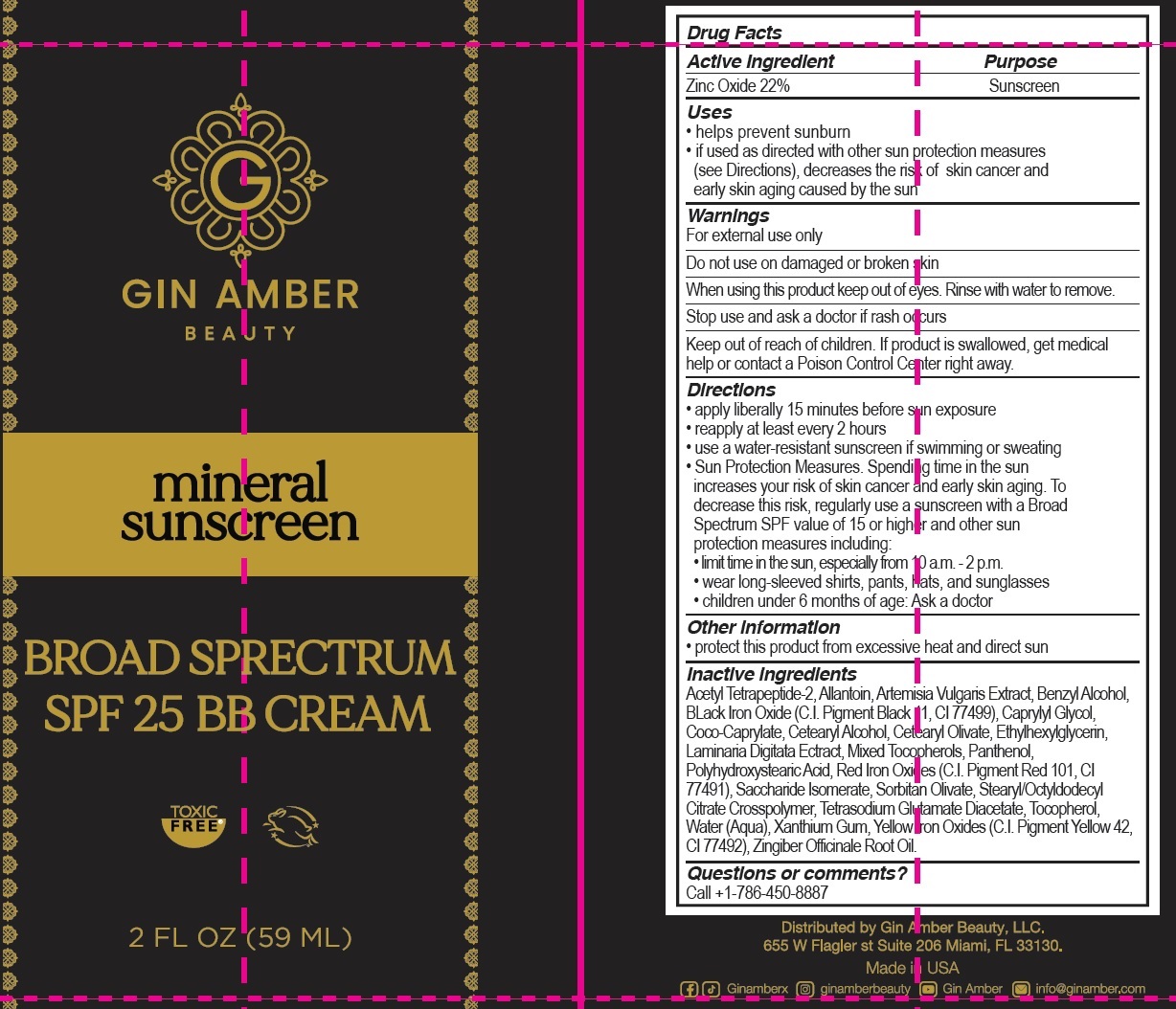 DRUG LABEL: Gin Amber Beauty Mineral Sunscreen Broad Spectrum SPF 25 BB Cream
NDC: 82618-320 | Form: CREAM
Manufacturer: Gin Amber Beauty LLC
Category: otc | Type: HUMAN OTC DRUG LABEL
Date: 20231114

ACTIVE INGREDIENTS: ZINC OXIDE 220 mg/1 mL
INACTIVE INGREDIENTS: ACETYL TETRAPEPTIDE-2; ALLANTOIN; BENZYL ALCOHOL; FERROSOFERRIC OXIDE; CAPRYLYL GLYCOL; COCO-CAPRYLATE; CETOSTEARYL ALCOHOL; CETEARYL OLIVATE; ETHYLHEXYLGLYCERIN; LAMINARIA DIGITATA; PANTHENOL; FERRIC OXIDE RED; SACCHARIDE ISOMERATE; SORBITAN OLIVATE; STEARYL/OCTYLDODECYL CITRATE CROSSPOLYMER; TETRASODIUM GLUTAMATE DIACETATE; TOCOPHEROL; WATER; XANTHAN GUM; FERRIC OXIDE YELLOW

Gin Amber Beauty Mineral Sunscreen Broad Spectrum SPF 25 BB Cream

Active Ingredient

Zinc Oxide 22%

Purpose

Sunscreen

Uses

• helps prevent sunburn • if used as directed with other sun protection measures (see Directions), decreases the risk of skin cancer and early skin aging caused by the sun

Warnings

For external use only

Do not use

on damaged or broken skin

When using this product

keep out of eyes. Rinse with water to remove.

Stop use and ask a doctor

if rash occurs

Keep out of reach of children.

If product is swallowed, get medical help or contact a Poison Control Center right away.

Directions

• apply liberally 15 minutes before sun exposure • reapply at least every 2 hours • use a water-resistant sunscreen if swimming or sweating • Sun Protection Measures. Spending time in the sun increases your risk of skin cancer and early skin aging. To decrease this risk, regularly use a sunscreen with a Broad Spectrum SPF value of 15 or higher and other sun protection measures including: • limit time in the sun, especially from 10 a.m. - 2 p.m. • wear long-sleeved shirts, pants, hats, and sunglasses • children under 6 months of age: Ask a doctor

Other information

• protect this product from excessive heat and direct sun

Inactive ingredients

Acetyl Tetrapeptide-2, Allantoin, Artemisia Vulgaris Extract, Benzyl Alcohol, BLack Iron Oxide (C.I. Pigment Black 11, CI 77499), Caprylyl Glycol, Coco-Caprylate, Cetearyl Alcohol, Cetearyl Olivate, Ethylhexylglycerin, Laminaria Digitata Ectract, Mixed Tocopherols, Panthenol, Polyhydroxystearic Acid, Red Iron Oxides (C.I. Pigment Red 101, CI 77491), Saccharide Isomerate, Sorbitan Olivate, Stearyl/Octyldodecyl Citrate Crosspolymer, Tetrasodium Glutamate Diacetate, Tocopherol, Water (Aqua), Xanthium Gum, Yellow Iron Oxides (C.I. Pigment Yellow 42, CI 77492), Zingiber Officinale Root Oil.

Questions or comments?

Call +1-786-450-8887